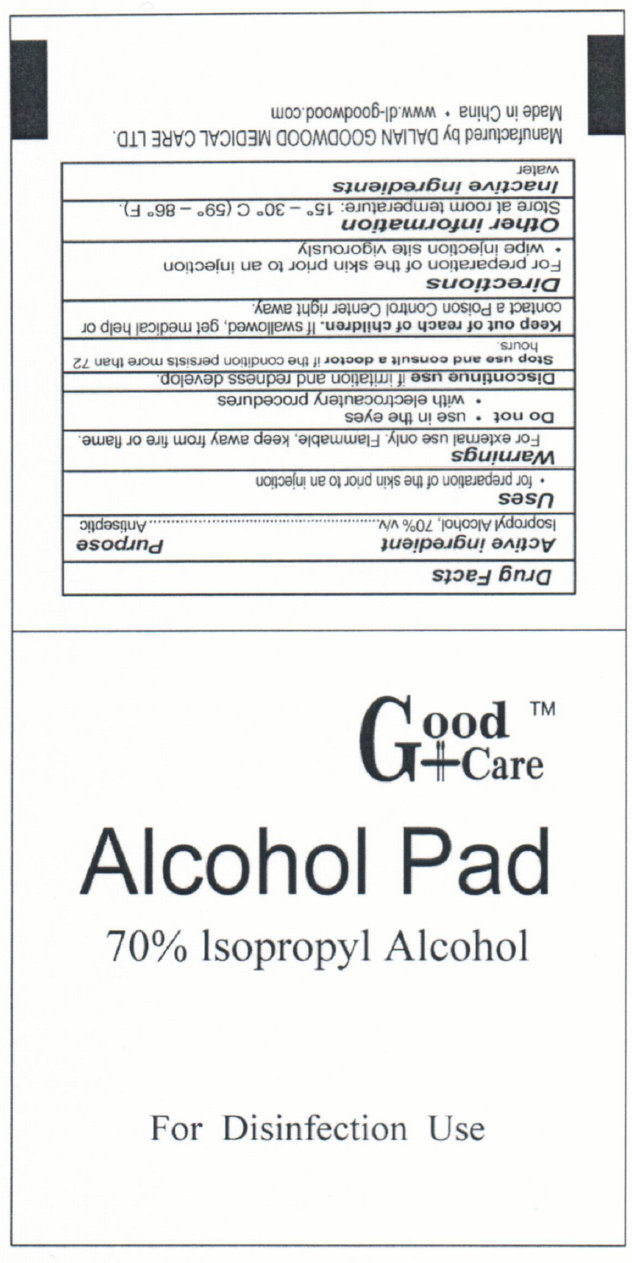 DRUG LABEL: Good Care Alcohol Pad
NDC: 50685-006 | Form: SWAB
Manufacturer: Dalian Goodwood Medical Care Ltd.
Category: otc | Type: HUMAN OTC DRUG LABEL
Date: 20230525

ACTIVE INGREDIENTS: ISOPROPYL ALCOHOL 70 g/100 g
INACTIVE INGREDIENTS: WATER

Good Care Alcohol Pad 70% Isopropyl Alcohol

Active Ingredient

Isopropyl Alcohol, 70% v/v

Purpose

Antiseptic

Uses

- for preparation of the skin prior to an injection

Warnings

For external use only. Flammable, keep away from fire or flame

Do not use in the eyes with electrocautery procedures

Discontinue use if irritation and redness develop.

Stop use and consult a doctor if the condition persists more than 72 hours.

Keep out of reach of children. If swallowed, get medical help or contact a Poison Control Center right away.

Directions

For preparation of the skin prior to an injection

- wipe injection site vigorously

Other information

Store at room temperature: 15 degrees - 30 degrees C (59 degrees - 86 degrees F)

Inactive ingredients

water

Manufactured by DALIAN GOODWOOD MEDICAL CARE LTD.
Made in China www.dl-goodwood.com

PACKAGE LABEL

Good Care

Alcohol Pad
70% Isopropyl Alcohol

For Disinfection Use